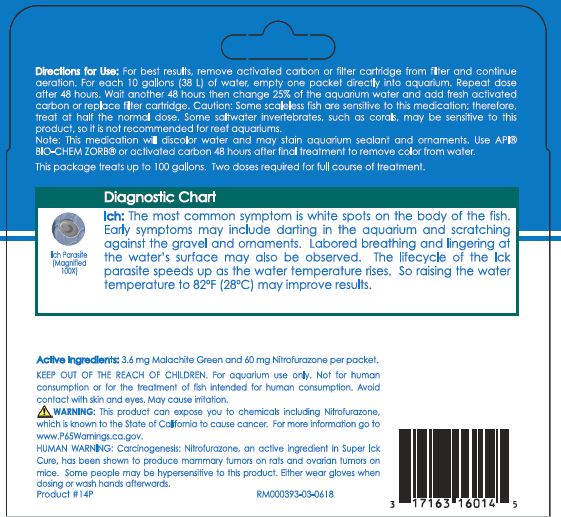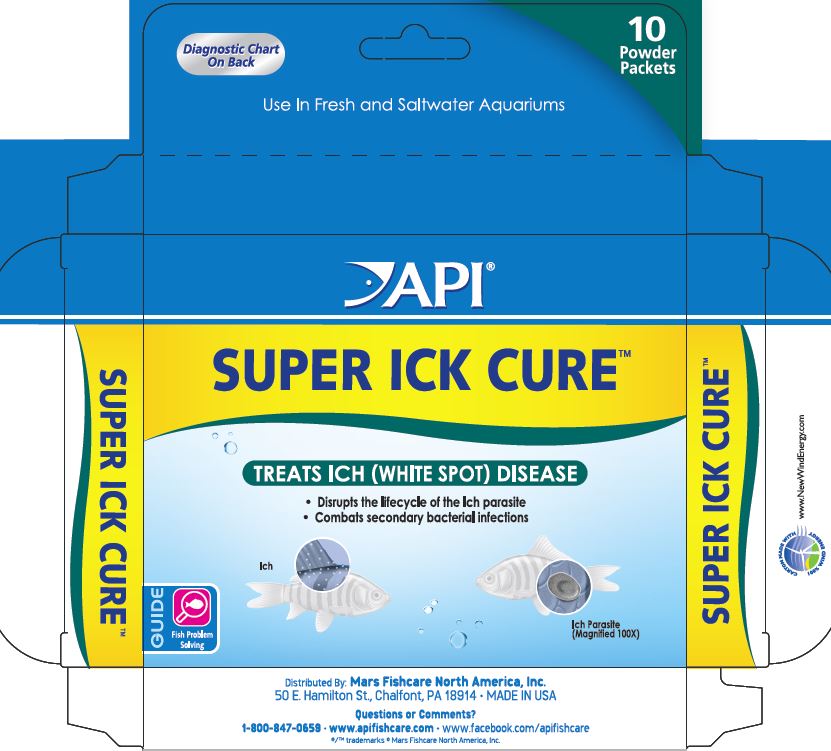 DRUG LABEL: API Super Ick Cure
NDC: 17163-512 | Form: POWDER
Manufacturer: MARS FISHCARE NORTH AMERICA, INC.
Category: animal | Type: OTC ANIMAL DRUG LABEL
Date: 20211229

ACTIVE INGREDIENTS: NITROFURAZONE 60 mg/2 g; MALACHITE GREEN 3.6 mg/2 g
INACTIVE INGREDIENTS: SODIUM CHLORIDE; SILICON DIOXIDE

Drug Label

ACTIVE INGREDIENT

Active Ingredients: 3.6 mg Malachite Green and 60 mg Nitrofurazone per packet.

DOSAGE AND ADMINISTRATION

Directions for Use:
For best results, remove activated carbon or filter cartridge from filter and continue aeration.
For each 10 gallons (38 L) of water, empty one packet directly into aquarium.
Repeat dose after 48 hours.
Wait another 48 hours then change 25% of the aquarium water and add fresh activated carbon or replace filter cartridge.
Caution: Some scaleless fish our sensitive to this medication; therefore,start at half the normal dose.
Some saltwater invertebrates, such as corals, may be sensitive to this product, so it is not recommended for reef aquariums.
Note: this medication will discolor water and may stain aquarium sealant and ornaments. Use API BIO-CHEM ZORB or activated carbon 48 hours after final treatment to remove color from water.
This package treats up to 100 gallons.
Two doses required for full course of treatment.

INDICATIONS AND USAGE

Diagnostic Chart
Ich:
The most common symptom is white spots on the body of the fish. Early symptom is white spots on body of the fish. Early Symptoms may include darting in the aquarium and scratching against the gravel and ornaments. Labored breathing and lingering at the water's surface may also be observed. The lifecycle of the Ick parasite speeds up as the water temperature rises. So raising the water temperature to 82 F (28 C) may improve results.

WARNINGS AND PRECAUTIONS

KEEP OUT OF THE REACH OF CHILDREN.
For aquarium use only.
Not for human consumption or for the treatment of fish intended for human consumption.
Avoid contact with skin and eyes.
May cause irritation.
! WARNING:
This product can expose you to chemicals including Nitrofurazone, which is known to the State of California to cause cancer.
For more information go to www.P65Warnings.ca.gov.
HUMAN WARNING:
Carcinogenesis:
Nitrofurazone, an active ingredient in Super Ick Cure, has been shown to produce mammary tumors on rats and ovarian tumors on mice.
Some people may be hypersensitive to this product.
Either wear gloves when dosing or wash hands afterwards.

PACKAGE LABEL

Diagnostic Chart
On Back
10
Powder
Packets
Use In Fresh and Saltwater Aquariums
API
SUPER ICK CURE
TREATS ICH (WHITE SPOT) DISEASE
Disrupts the lifecycle of the Ich parasite
Combats secondary bacterial infections
Ich
Ich Parasite
GUIDE
Fish Problem
Solving